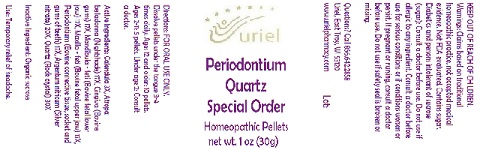 DRUG LABEL: Periodontium Quartz Special Order
NDC: 48951-8234 | Form: PELLET
Manufacturer: Uriel Pharmacy Inc.
Category: homeopathic | Type: HUMAN OTC DRUG LABEL
Date: 20180605

ACTIVE INGREDIENTS: CALENDULA OFFICINALIS FLOWERING TOP 3 [hp_X]/1 1; ATROPA BELLADONNA 17 [hp_X]/1 1; BEEF TONGUE 17 [hp_X]/1 1; BOS TAURUS BONE 17 [hp_X]/1 1; SUS SCROFA TOOTH 17 [hp_X]/1 1; SILVER 20 [hp_X]/1 1; SILICON DIOXIDE 30 [hp_X]/1 1
INACTIVE INGREDIENTS: SUCROSE

Periodontium Quartz Special Order

INDICATIONS AND USAGE

Directions: FOR ORAL USE ONLY.

DOSAGE AND ADMINISTRATION

Dissolve pellets under the tongue 3-4 times daily. Ages 12 and older: 10 pellets. Ages 2-11: 5 pellets. Under age 2: Consult a doctor.

ACTIVE INGREDIENT

Active Ingredients: Calendula ex herba 3X, Atropa belladonna ex herba 17X, Gingiva 17X, Mandibula (feti) 17X, Maxilla (feti) 17X, Periodontium 17X, Argentum nitricum 20X, Quartz 30X

Inactive Ingredient: Organic sucrose

PURPOSE

Use: Temporary relief of headache.

KEEP OUT OF REACH OF CHILDREN.

WARNINGS

Warnings: Claims based on traditional homeopathic practice, not accepted medical evidence. Not FDA evaluated. Contains sugar. Diabetics and persons intolerant of sucrose (sugar): Consult a doctor before use. Do not use if allergic to any ingredient. Consult a doctor before use for serious conditions or if conditions worsen or persist. If pregnant or nursing, consult a doctor before use. Do not use if safety seal is broken or missing.

QUESTIONS

Questions? Call 866.642.2858 Uriel, East Troy, WI 53120 www.urielpharmacy.com